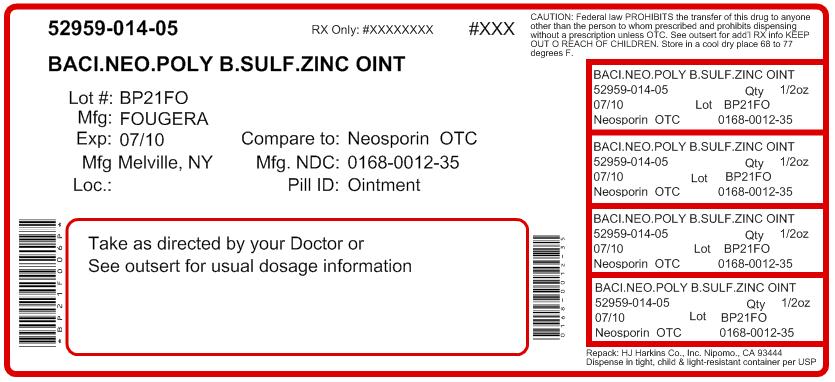 DRUG LABEL: Neomycin and Polymyxin B Sulfates and Bacitracin Zinc
NDC: 52959-014 | Form: OINTMENT
Manufacturer: H.J. Harkins Company, Inc.
Category: otc | Type: HUMAN OTC DRUG LABEL
Date: 20110830

ACTIVE INGREDIENTS: Bacitracin Zinc 400 [USP'U]/1 g; Neomycin Sulfate 5 mg/1 g; Polymyxin B Sulfate 5000 [USP'U]/1 g
INACTIVE INGREDIENTS: petrolatum

Fougera ® Triple Antibiotic Ointment
(Neomycin and Polymyxin B Sulfates and Bacitracin Zinc Ointment USP)

Active ingredients (in each gram)

Neomycin Sulfate (5 mg equivalent to 3.5 mg neomycin base)
Polymyxin B Sulfate (equal to 5.000 polymyxin B units)
Bacitracin Zinc (equal to 400 bacitracin units)

Purpose

Antibiotic
Antibiotic
Antibiotic

Uses

first aid to help prevent infection in

- minor cuts
- scopes
- bums

For external use only

Do not use

- in the eyes
- over large areas of the body
- if you are allergic to any of the ingredients

Ask a doctor before use in case of deep or puncture wounds, animal bites or serous bums

When using this product do not use longer than 1 week unless directed by a doctor

Stop use and ask a doctor if

- the condition persists or gets worse
- if a rash or other allergic reaction develops

Keep out of reach of children.

If swallowed, get medical help or contact a Poison Control Center right away.

Directions

- clean the affected area
- apply a small amount of this product (an amount equal to the surface area of the tip of a finger) on the area 1 to 3 times daily
- may be covered with a sterile bandage

Other information

- do not use if seal is punctured or is not visible. To open, reverse cap to puncture seal
- store at room temperature
- see crimp of tube for Lot No. and Exp, date

Inactive ingredient white petrolatum

Questions or comments? call toll free 1-800-645-9833

PACKAGE LABEL – PRINCIPAL DISPLAY PANEL – 1/2 Oz CONTAINER

Fougera®

NDC 52959-014

Triple Antibiotic Ointment
(Neomycin and Polymyxin B Sulfates and Bacitracin Zinc Ointment USP)

Repacked by:

H.J. Harkins Company, Inc.
513 Sandydale Drive
Nipomo, CA